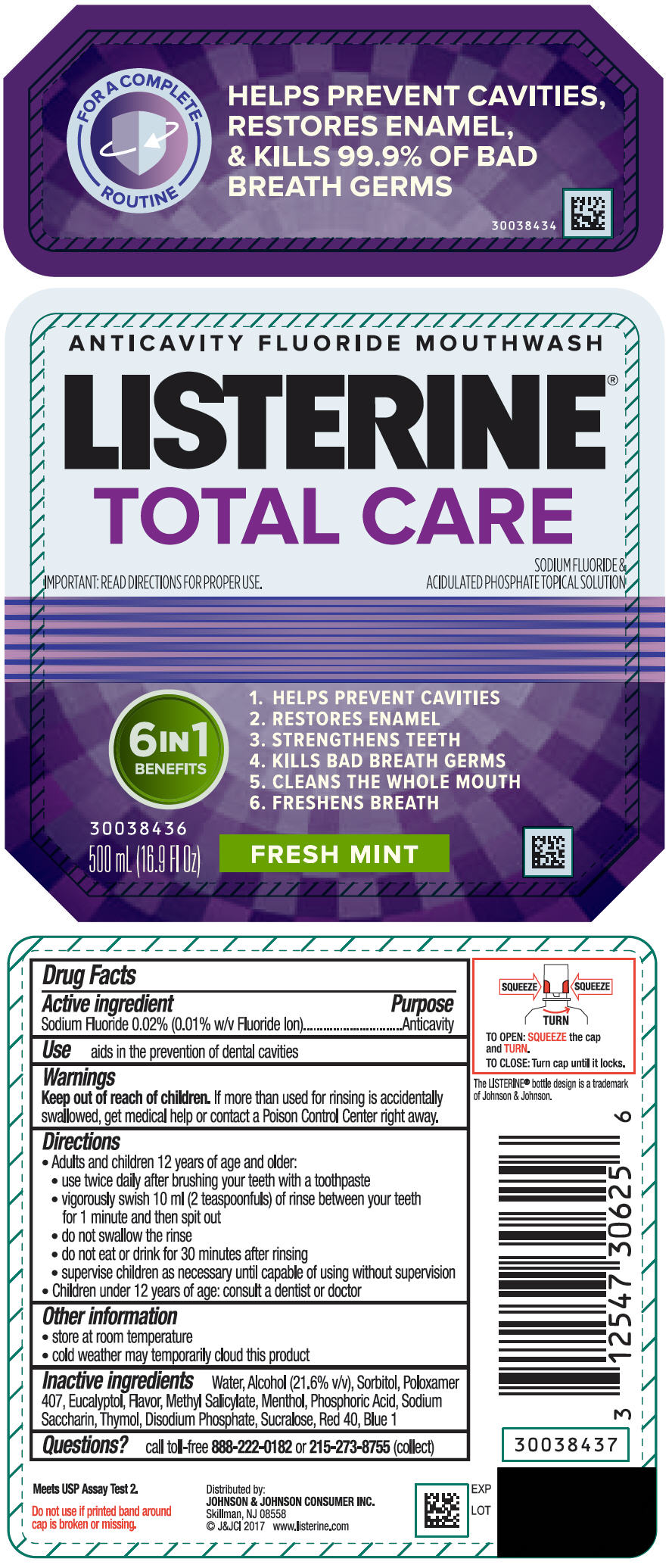 DRUG LABEL: Listerine Total Care Fresh Mint
NDC: 69968-0178 | Form: MOUTHWASH
Manufacturer: Kenvue Brands LLC
Category: otc | Type: HUMAN OTC DRUG LABEL
Date: 20241111

ACTIVE INGREDIENTS: SODIUM FLUORIDE 0.1 mg/1 mL
INACTIVE INGREDIENTS: WATER; ALCOHOL; SORBITOL; POLOXAMER 407; PHOSPHORIC ACID; EUCALYPTOL; THYMOL; METHYL SALICYLATE; SACCHARIN SODIUM; MENTHOL, UNSPECIFIED FORM; SODIUM PHOSPHATE, DIBASIC, ANHYDROUS; SUCRALOSE; FD&C RED NO. 40; FD&C BLUE NO. 1

LISTERINE® TOTAL CARE ANTICAVITY MOUTHWASH FRESH MINT

Drug Facts

Active ingredient

Sodium fluoride 0.02% (0.01% w/v fluoride ion)

Purpose

Anticavity

Use

aids in the prevention of dental cavities

Warnings

Keep out of reach of children. If more than used for rinsing is accidentally swallowed, get medical help or contact a Poison Control Center right away .

Directions

- Adults and children 6 years of age and older:
  - use twice daily after brushing your teeth with a toothpaste
  - vigorously swish 10mL (2 teaspoonfuls) of rinse between your teeth for 1 minute and then spit out
  - do not swallow the rinse
  - do not eat or drink for 30 minutes after rinsing
  - supervise children as necessary until capable of using without supervision
- Children under 6 years of age: consult a dentist or doctor

Other information

- store at room temperature
- cold weather may temporarily cloud this product

Inactive ingredients

Water, Alcohol (21.6% v/v), Sorbitol, Poloxamer 407, Eucalyptol, Flavor, Methyl Salicylate, Menthol, Phosphoric Acid, Sodium Saccharin, Thymol, Disodium Phosphate, Sucralose, Red 40, Blue 1

Questions?

Call toll-free 888-222-0182 or 215-273-8755 (collect)

Dist: Johnson & Johnson Healthcare Products
Division of McNEIL-PPC, Inc.
Skillman, NJ 08558-9418

PRINCIPAL DISPLAY PANEL - 500 mL Bottle Label

ANTICAVITY FLOURIDE MOUTHWASH

LISTERINE®

TOTAL CARE

IMPORTANT: READ DIRECTIONS FOR PROPER USE.

SODIUM FLUORIDE &

ACIDULATED PHOSPHATE TOPICAL SOLUTION

6 IN 1

BENEFITS

- HELPS PREVENT CAVITIES
- RESTORES ENAMEL
- STRENGTHENS TEETH
- KILLS BAD BREATH GERMS
- CLEANS THE WHOLE MOUTH
- FRESHENS BREATH

500 mL (16.9 Fl Oz) FRESH MINT